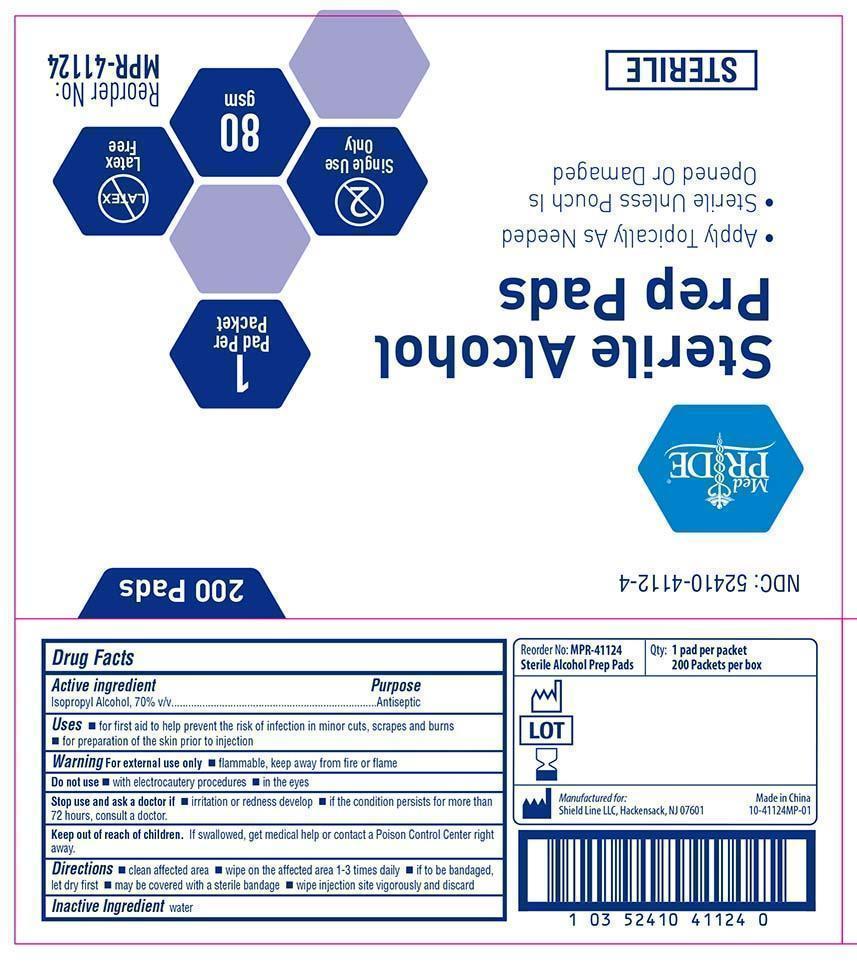 DRUG LABEL: MedPride
NDC: 52410-4112 | Form: CLOTH
Manufacturer: Shield Line LLC
Category: otc | Type: HUMAN OTC DRUG LABEL
Date: 20171218

ACTIVE INGREDIENTS: ISOPROPYL ALCOHOL 0.7 mL/1 1
INACTIVE INGREDIENTS: WATER

Drug Facts

Active Ingredient

Isopropyl Alcohol 70% v/v

Purpose

Antiseptic

Uses

■ for first aid to help prevent the risk of infection in minor cuts, scrapes and burns ■ for preparation of skin prior to injection

Warnings

For external use only
■ flammable, keep away from fire or flame

Do not use

■ with electrocautery procedures ■ in the eyes

Stop use and ask a doctor if

■ if irritation and redness develops ■ if the condition persist for more than 72 hours consult a doctor.

Keep out of reach of children

If swallowed, get medical help or contact a Poison Control Center right away.

Directions

■ clean affected area ■ wipe on the affected area 1-3 times daily ■ if to be bandaged dry first ■may be covered with a sterile bandage ■wipe injection site vigorously and discard

Inactive Ingredient

water